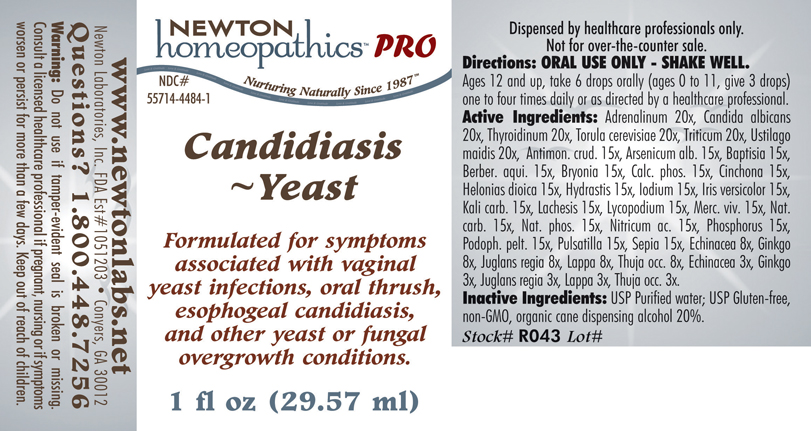 DRUG LABEL: Candidiasis Yeast 
NDC: 55714-4484 | Form: LIQUID
Manufacturer: Newton Laboratories, Inc.
Category: homeopathic | Type: HUMAN PRESCRIPTION DRUG LABEL
Date: 20110601

ACTIVE INGREDIENTS: Epinephrine 20 [hp_X]/1 mL; Candida Albicans 20 [hp_X]/1 mL; Thyroid, Unspecified 20 [hp_X]/1 mL; Saccharomyces Cerevisiae 20 [hp_X]/1 mL; Elymus Repens Top 20 [hp_X]/1 mL; Ustilago Maydis 20 [hp_X]/1 mL; Antimony Trisulfide 15 [hp_X]/1 mL; Arsenic Trioxide 15 [hp_X]/1 mL; Baptisia Tinctoria Root 15 [hp_X]/1 mL; Mahonia Aquifolium Root Bark 15 [hp_X]/1 mL; Bryonia Alba Root 15 [hp_X]/1 mL; Tribasic Calcium Phosphate 15 [hp_X]/1 mL; Cinchona Officinalis Bark 15 [hp_X]/1 mL; Chamaelirium Luteum Root 15 [hp_X]/1 mL; Goldenseal 15 [hp_X]/1 mL; Iodine 15 [hp_X]/1 mL; Iris Versicolor Root 15 [hp_X]/1 mL; Potassium Carbonate 15 [hp_X]/1 mL; Lachesis Muta Venom 15 [hp_X]/1 mL; Lycopodium Clavatum Spore 15 [hp_X]/1 mL; Mercury 15 [hp_X]/1 mL; Sodium Carbonate 15 [hp_X]/1 mL; Sodium Phosphate, Dibasic, Heptahydrate 15 [hp_X]/1 mL; Nitric Acid 15 [hp_X]/1 mL; Phosphorus 15 [hp_X]/1 mL; Podophyllum 15 [hp_X]/1 mL; Pulsatilla Vulgaris 15 [hp_X]/1 mL; Sepia Officinalis Juice 15 [hp_X]/1 mL; Echinacea, Unspecified 8 [hp_X]/1 mL; Ginkgo 8 [hp_X]/1 mL; English Walnut 8 [hp_X]/1 mL; Arctium Lappa Root 8 [hp_X]/1 mL; Thuja Occidentalis Leafy Twig 8 [hp_X]/1 mL; Echinacea, Unspecified 3 [hp_X]/1 mL; Ginkgo 3 [hp_X]/1 mL; English Walnut 3 [hp_X]/1 mL; Arctium Lappa Root 3 [hp_X]/1 mL; Thuja Occidentalis Leafy Twig 3 [hp_X]/1 mL
INACTIVE INGREDIENTS: Alcohol

Candidiasis~Yeast

PRODUCT NAME & INDICATIONS SECTION

Candida~Yeast Formulated for symptoms associated with vaginal yeast infections, oral thrush, esophogeal candidiasis, and other yeast or fungal overgrowth conditions.

DOSAGE & DIRECTION SECTION

Directions: ORAL USE ONLY - SHAKE WELL. Ages 12 and up, take 6 drops orally (ages 0 to 11, give 3 drops) one to four times daily or as directed by a healthcare professional.

ACTIVE INGREDIENT SECTION

Adrenalinum 20x, Candida albicans 20x, Thyroidinum 20x, Torula cerevisiae 20x, Triticum 20x, Ustilago maidis 20x, Antimon. crud. 15x, Arsenicum alb. 15x, Baptisia 15x, Berber. aqui. 15x, Bryonia 15x, Calc. phos. 15x, Cinchona 15x, Helonias dioica 15x, Hydrastis 15x, Iodium 15x, Iris versicolor 15x, Kali carb. 15x, Lachesis 15x, Lycopodium 15x, Merc. viv. 15x, Nat. carb. 15x, Nat. phos. 15x, Nitricum ac. 15x, Phosphorus 15x, Podoph. pelt. 15x, Pulsatilla 15x, Sepia 15x, Echinacea 8x, Ginkgo 8x, Juglans regia 8x, Lappa 8x, Thuja occ. 8x, Echinacea 3x, Ginkgo 3x, Juglans regia 3x, Lappa 3x, Thuja occ. 3x.

PURPOSE SECTION

Formulated for symptoms associated with vaginal yeast infections, oral thrush, esophogeal candidiasis, and other yeast or fungal overgrowth conditions.

INACTIVE INGREDIENT SECTION

USP Purified Water; USP Gluten-free, non-GMO, organic cane dispensing alcohol 20%.

QUESTIONS? SECTION

www.newtonlabs.net Newton Laboratories, Inc. FDA Est # 1051203 - Conyers, GA 30012
Questions? 1.800.448.7256

WARNINGS SECTION

Warning: Do not use if tamper - evident seal is broken or missing. Consult a licensed healthcare professional if pregnant, nursing or if symptoms worsen or persist for more than a few days. Keep out of reach of children.

OTC - PREGNANCY OR BREAST FEEDING SECTION

Consult a licensed healthcare professional if pregnant or nursing or if symptoms worsen or persist for more than a few days.

OTC - KEEP OUT OF REACH OF CHILDREN SECTION

Keep out of reach of children.